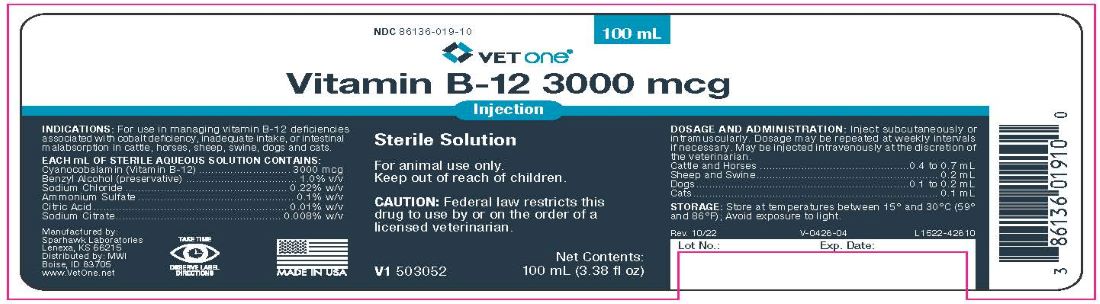 DRUG LABEL: Vitamin B12
NDC: 86136-019 | Form: INJECTION, SOLUTION
Manufacturer: MWI/Vet One
Category: animal | Type: PRESCRIPTION ANIMAL DRUG LABEL
Date: 20231218

ACTIVE INGREDIENTS: CYANOCOBALAMIN 3000 ug/1 mL
INACTIVE INGREDIENTS: WATER

Vitamin B12 3000 mcg

INDICATIONS AND USAGE

3000 mcg/mL

Sterile Solution

For animal use only.

Keep out of reach of children.

CAUTION: Federal law restricts this drug to use by or on the order of a licensed veterinarian.

INDICATIONS

For use as a supplemental nutritive source of vitamin B12 in cattle, horses, swine, sheep, dogs and cats.

CONTAINS

Each mL of sterile aqueous solution contains:

Cyanocobalamin (B12)..........3000 mcg

With sodium chloride 0.22% w/v, ammonium sulfate 0.1% w/v, citric acid 0.01% w/v, sodium citrate 0.008% w/v, and benzyl alcohol 1.0% v/v (preservative).

STORAGE

Store at controlled room temperature between 15°C and 30°C (59°F - 86°F).

Avoid exposure to light.

AVOID EXPOSURE TO LIGHT

DOSAGE AND ADMINISTRATION

Inject subcutaneously or intramuscularly. Dosage may be repeated at weekly intervals if necessary. May be injected intravenously at the discretion of the veterinarian.

Cattle and Horses ...............................................0.4 to 0.7 mL

Sheep and Swine......................................................... 0.2 mL

Dogs...................................................................0.1 to 0.2 mL

Cats............................................................................. 0.1 mL

TAKE TIME OBSERVE LABEL DIRECTIONS

PACKAGE LABEL

Vitamin B-12 3000 mcg

100 mL

Injection

Sterile Solution